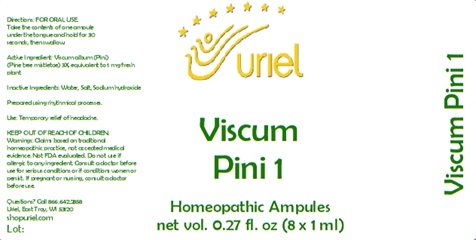 DRUG LABEL: Viscum Pini 1
NDC: 48951-9315 | Form: LIQUID
Manufacturer: Uriel Pharmacy Inc.
Category: homeopathic | Type: HUMAN OTC DRUG LABEL
Date: 20241203

ACTIVE INGREDIENTS: VISCUM ALBUM FRUITING TOP 3 [hp_X]/1 mL
INACTIVE INGREDIENTS: WATER; SODIUM CHLORIDE; SODIUM HYDROXIDE

Viscum Pini 1

INDICATIONS AND USAGE

Directions: FOR ORAL USE.

DOSAGE AND ADMINISTRATION

Take the contents of one ampule under the tongue and hold for 30 seconds, then swallow.

Active Ingredient: Viscum album Pini (Pine tree mistletoe) 3X, equivalent to 1 mg fresh plant

Inactive Ingredients: Water, Salt, Sodium Hydroxide

Prepared using rhythmical processes.

PURPOSE

Use: Temporary relief of headache.

KEEP OUT OF REACH OF CHILDREN.

WARNINGS

Warnings: Claims based on traditional homeopathic practice, not accepted medical evidence. Not FDA evaluated. Do not use if allergic to any ingredient. Consult a doctor before use for serious conditions or if conditions worsen or persist. If pregnant or nursing, consult a doctor before use.

QUESTIONS

Questions? Call 866.642.2858 Uriel, East Troy, WI 53120 shopuriel.com Lot: